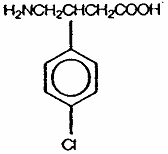 DRUG LABEL: Unknown
Manufacturer: Schwarz Pharma
Category: prescription | Type: Human prescription drug label
Date: 20060104

KEMSTRO™ (baclofen orally disintegrating tablets)

Description

KEMSTRO™ (baclofen orally disintegrating tablets) is a muscle relaxant and antispastic. Baclofen USP is a white to off-white, odorless or practically odorless crystalline powder. It is slightly soluble in water, very slightly soluble in methanol, and insoluble in chloroform. Its chemical name is 4-amino-3-(4-chlorophenyl)-butanoic acid. The molecular weight of baclofen is 213.66 and the empirical formula is C10H12CINO2. The structural formula is represented below:

KEMSTRO™ is available as 10 mg and 20 mg orally disintegrating tablets. Each orally disintegrating tablet also contains as inactive ingredients: aspartame, colloidal silicon dioxide, crospovidone, magnesium stearate, mannitol, microcrystalline cellulose, natural and artificial orange flavor and povidone.

Clinical Pharmacology

The precise mechanism of action of baclofen is not fully known. Baclofen is capable of inhibiting both monosynaptic and polysynaptic reflexes at the spinal level, possibly by hyperpolarization of afferent terminals, although actions at supraspinal sites may also occur and contribute to its clinical effect. Although baclofen is an analog of the putative inhibitory neurotransmitter gamma-amino-butyric acid (GABA), there is no conclusive evidence that actions on GABA systems are involved in the production of its clinical effects. In studies with animals, baclofen has been shown to have general CNS depressant properties as indicated by the production of sedation with tolerance, somnolence, ataxia, and respiratory and cardiovascular depression.

Pharmacokinetics

Absorption

Baclofen is rapidly and extensively absorbed. Absorption may be dose-dependent, being reduced with increasing doses. KEMSTRO™ given with or without water is bioequivalent to the baclofen conventional tablet. Thus KEMSTRO™ can be placed on the tongue until it disintegrates and then be swallowed with or without water. Following a single 20 mg oral dose of KEMSTRO™, the peak plasma concentration was reached about 1½ hours after administration.

Distribution

The apparent volume of distribution is 59 liters. Baclofen does not readily cross the blood-brain barrier. Plasma protein binding is approximately 30%.

Metabolism

In a study using radiolabeled baclofen, approximately 85% of the dose was excreted unchanged in the urine and feces. About 15% of the dose was metabolized, primarily by deamination. The γ-hydroxy metabolite, 3-(p-chlorophenyl)-4-hydroxybutyric acid, is formed after deamination of baclofen.

Excretion

Baclofen is rapidly and extensively eliminated. There is a relatively large intersubject variation in elimination. Baclofen is excreted primarily by the kidney as unchanged drug; 70 - 80% of a dose appears in the urine as unchanged drug. The remainder is excreted as unchanged drug in the feces or as metabolites in the urine and feces. Excretion is complete within 72 hours after administration. The elimination half-life of KEMSTRO™ is approximately 5½ hours. Total systemic clearance is 180 mL/min and renal clearance is 103 mL/min.

Special Populations Elderly

The pharmacokinetics of baclofen tablets were evaluated in elderly patients (69-81 years) and in healthy younger subjects (23-53 years) after a single 10 mg dose. The Cmax was lower (119 ng/mL vs. 178 ng/mL) and the Tmax was longer (3 hours vs. 1 hour) in the elderly patients compared to the younger subjects. The AUCs were similar in the two groups. In this study, the elimination half-life was slightly prolonged in the elderly patients compared to the younger subjects, 4.43 hours vs. 3.75 hours, respectively.

Indications and Usage

KEMSTRO™ is useful for the alleviation of signs and symptoms of spasticity resulting from multiple sclerosis, particularly for the relief of flexor spasms and concomitant pain, clonus, and muscular rigidity.

Patients should have reversible spasticity so that treatment with KEMSTRO™ will aid in restoring residual function.

KEMSTRO™ may also be of some value in patients with spinal cord injuries and other spinal cord diseases.

KEMSTRO™ is not indicated in the treatment of skeletal muscle spasm resulting from rheumatic disorders.

The efficacy of KEMSTRO™ in stroke, cerebral palsy, and Parkinson's disease has not been established and, therefore, it is not recommended for these conditions.

Contraindications

KEMSTRO™ is contraindicated in patients who are hypersensitive to any component of this product.

Warning

Abrupt Drug Withdrawal

Hallucinations and seizures have occurred on abrupt withdrawal of baclofen. Therefore, except for serious adverse reactions, the dose should be reduced slowly when the drug is discontinued.

Impaired Renal Function

Because baclofen is primarily excreted unchanged by the kidneys, it should be given with caution and it may be necessary to reduce the dosage in patients with impaired renal function.

Stroke

Baclofen has not significantly benefited patients with stroke. These patients have also shown poor tolerability to the drug.

Precautions

General

Baclofen should be used with caution where spasticity is utilized to sustain upright posture and balance in locomotion or whenever spasticity is utilized to obtain increased function.

In patients with epilepsy, the clinical state and electroencephalogram should be monitored at regular intervals, since deterioration in seizure control and EEG have been reported occasionally in patients taking baclofen.

Information for patients

Because of the possibility of sedation, patients should be cautioned regarding the operation of automobiles or other dangerous machinery, and activities made hazardous by decreased alertness. Patients should also be cautioned that the central nervous system depressant effects of baclofen may be additive to those of alcohol and other CNS depressants.

Phenylketonurics

Phenylketonuric patients should be informed that KEMSTRO™ contains phenylalanine

3.9 mg per 10 mg orally disintegrating tablet and 7.9 mg per 20 mg orally disintegrating tablet.

Interactions

Drug interactions

The central nervous system depressant effects of baclofen may be additive to those of alcohol and other CNS depressants.

Carcinogenesis, mutagenesis, impairment of fertility

A dose-related increase in incidence of ovarian cysts and a less marked increase in enlarged and/or hemorrhagic adrenal glands was observed in female rats treated chronically with baclofen.

Ovarian cysts have been found by palpation in about 4% of the multiple sclerosis patients that were treated with baclofen for up to one year. In most cases these cysts disappeared spontaneously while patients continued to receive the drug. Ovarian cysts are estimated to occur spontaneously in approximately 1% to 5% of the normal female population.

Pregnancy

Pregnancy Category C. Baclofen has been shown to increase the incidence of omphaloceles (ventral hernias) in fetuses of rats given approximately 13 times the maximum dose recommended for human use, at a dose which caused significant reductions in food intake and weight gain in dams. This abnormality was not seen in mice or rabbits. There was also an increased incidence of incomplete sternebral ossification in fetuses of rats given approximately 13 times the maximum recommended human dose, and an increased incidence of unossified phalangeal nuclei of forelimbs and hindlimbs in fetuses of rabbits given approximately 7 times the maximum recommended human dose. In mice, no teratogenic effects were observed, although reductions in mean fetal weight with consequent delays in skeletal ossification were present when dams were given 17 or 34 times the human daily dose. There are no adequate and well-controlled studies in pregnant women. KEMSTRO™ should be used during pregnancy only if the potential benefit justifies the potential risk to the fetus.

Nursing mothers

It is not known whether this drug is excreted in human milk. Because many drugs are excreted in human milk, caution should be exercised when KEMSTRO™ is administered to a nursing woman.

Pediatric use

Safety and effectiveness in pediatric patients below the age of 12 have not been established.

Geriatric use

Clinical studies of baclofen did not include sufficient numbers of subjects aged 65 and over to determine whether they respond differently from younger subjects. In general, dose selection for an elderly patient should be cautious, usually starting at the low end of the dosing range, reflecting the greater frequency of decreased hepatic, renal, or cardiac function, and of concomitant disease or other drug therapy.

This drug is known to be substantially excreted by the kidney, and the risk of toxic reactions to this drug may be greater in patients with impaired renal function. Because elderly patients are more likely to have decreased renal function, care should be taken in dose selection, and it may be useful to monitor renal function.

Sedating drugs may cause confusion and over-sedation in the elderly; elderly patients generally should be started on low doses of KEMSTRO™ and observed closely.

Adverse Reactions

The most common adverse reaction during treatment with baclofen is transient drowsiness (10-63%). In one controlled study of 175 patients, transient drowsiness was observed in 63% of those receiving baclofen tablets compared to 36% of those in the placebo group. Other common adverse reactions are dizziness (5-15%), weakness (5-15%) and fatigue (2-4%). Others reported:

Neuropsychiatric: Confusion (1-11%), headache (4-8%), insomnia (2-7%); and, rarely, euphoria, excitement, depression, hallucinations, paresthesia, muscle pain, tinnitus, slurred speech, coordination disorder, tremor, rigidity, dystonia, ataxia, blurred vision, nystagmus, strabismus, miosis, mydriasis, diplopia, dysarthria, epileptic seizure.

Cardiovascular: Hypotension (0-9%). Rare instances of dyspnea, palpitation, chest pain, syncope.

Gastrointestinal: Nausea (4-12%), constipation (2-6%); and, rarely, dry mouth, anorexia, taste disorder, abdominal pain, vomiting, diarrhea, and positive test for occult blood in stool.

Genitourinary: Urinary frequency (2-6%); and, rarely, enuresis, urinary retention, dysuria, impotence, inability to ejaculate, nocturia, hematuria.

Other: Instances of rash, pruritus, ankle edema, excessive perspiration, weight gain, nasal congestion.

Some of the CNS and genitourinary symptoms may be related to the underlying disease rather than to drug therapy. The following laboratory tests have been found to be abnormal in a few patients receiving baclofen: increased SGOT, elevated alkaline phosphatase, and elevation of blood sugar.

The adverse experience profile seen with KEMSTRO™ was similar to that seen with baclofen tablets.

Drug Abuse and Dependence

Overdosage

Signs and Symptoms

Vomiting, muscular hypotonia, drowsiness, accommodation disorders, coma, respiratory depression, and seizures.

Treatment

In the alert patient, empty the stomach promptly by induced emesis followed by lavage. In the obtunded patient, secure the airway with a cuffed endotracheal tube before beginning lavage (do not induce emesis). Maintain adequate respiratory exchange, do not use respiratory stimulants. It is unknown what effect hemodialysis or peritoneal dialysis has on the serum concentration of baclofen.

Dosage and Administration

The determination of optimal dosage requires individual titration. Start therapy at a low dosage and increase gradually until optimum effect is achieved (usually between 40-80 mg daily).

The following dosage titration schedule is suggested:

5 mg three times a day for 3 days

10 mg three times a day for 3 days

15 mg three times a day for 3 days

20 mg three times a day for 3 days

Thereafter additional increases may be necessary but the total daily dose should not exceed a maximum of 80 mg daily (20 mg four times a day).

The lowest dose compatible with an optimal response is recommended. If benefits are not evident after a reasonable trial period, patients should be slowly withdrawn from the drug (see WARNINGS, Abrupt Drug Withdrawal).

Administration

Using dry hands, the patient should be instructed to place the tablet on the tongue, where it will disintegrate and can then be swallowed with or without water.

Patients with Renal Impairment

Because baclofen is primarily excreted unchanged by the kidneys, it should be given with caution and it may be necessary to reduce the dosage in patients with impaired renal function.

How Supplied

KEMSTRO™ (baclofen orally disintegrating tablets) 10 mg are white, round, orange-flavored, scored and engraved “10” on the unscored side and “SP” above and “351” below the score on the other side. They are supplied as follows:

Bottles of 100NDC 0091-3351-01

KEMSTRO™ (baclofen orally disintegrating tablets) 20 mg are white, round, orange-flavored, scored and engraved “20” on the unscored side and “SP” above and “352” below the score on the other side. They are supplied as follows:

Bottles of 100NDC 0091-3352-01

Dispense in a tight container as defined in the USP/NF with a child-resistant closure.

Store at controlled room temperature 20º- 25º (68º- 77º); excursions permitted between

15º- 30º (59º- 86º). Protect from moisture.

Manufactured for:
Schwarz Pharma

Milwaukee, WI 53201, USA

By:

CIMA LABS INC.®

Eden Prairie, MN 55344, USA

KEMSTRO™ uses CIMA U.S. Patent Nos. 6,024,981 and 6,221,392.

PC4536A

Rev. 01/04